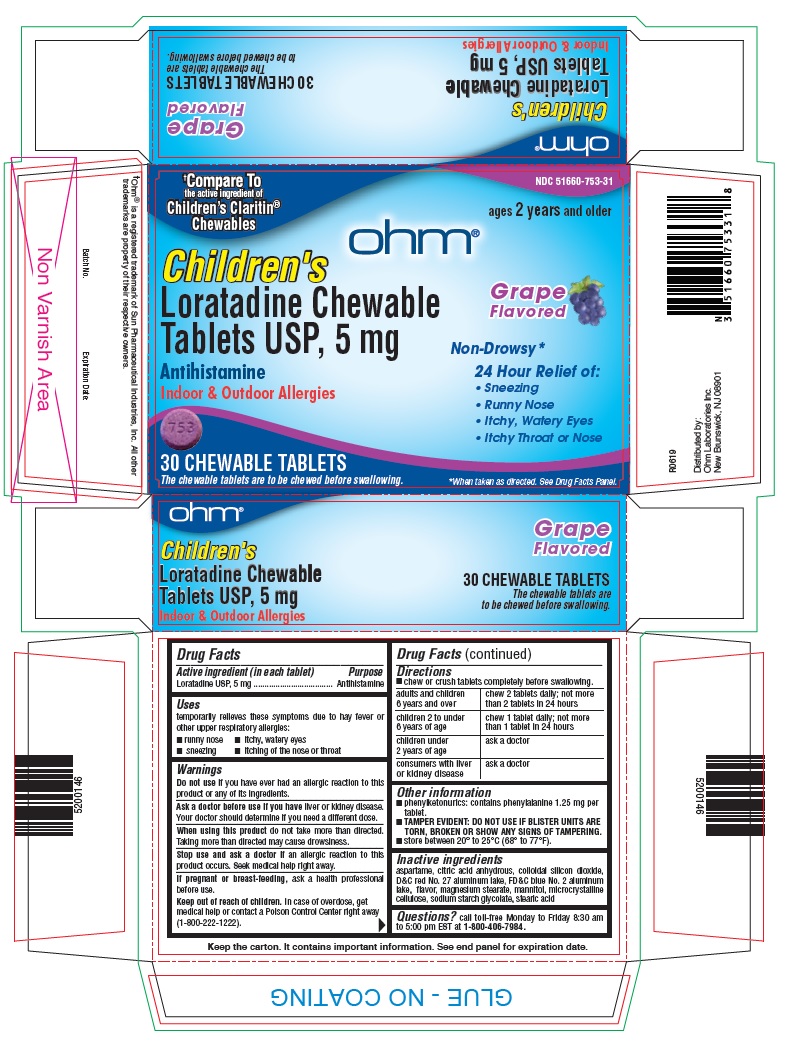 DRUG LABEL: Loratadine
NDC: 51660-753 | Form: TABLET, CHEWABLE
Manufacturer: Ohm Laboratories Inc.
Category: otc | Type: HUMAN OTC DRUG LABEL
Date: 20190717

ACTIVE INGREDIENTS: LORATADINE 5 mg/1 1
INACTIVE INGREDIENTS: ASPARTAME; ANHYDROUS CITRIC ACID; SILICON DIOXIDE; D&C RED NO. 27; FD&C BLUE NO. 2; MAGNESIUM STEARATE; MANNITOL; MICROCRYSTALLINE CELLULOSE; STEARIC ACID; SODIUM STARCH GLYCOLATE TYPE A POTATO

Drug Facts

Active ingredient (in each tablet)

Loratadine USP, 5 mg

Purpose

Antihistamine

Uses

temporarily relieves these symptoms due to hay fever or other upper respiratory allergies:

- runny nose
- sneezing
- itchy, watery eyes
- itching of the nose or throat

Warnings

Do not use if you have ever had an allergic reaction to this product or any of its ingredients.

Ask a doctorbefore use if you have liver or kidney disease. Your doctor should determine if you need a different dose.

When using this product do not take more than directed. Taking more than directed may cause drowsiness.

Stop use and ask a doctor if an allergic reaction to this product occurs. Seek medical help right away.

If pregnant or breast-feeding, ask a health professional before.

Keep Out of Reach of Children

In case of overdose, get medical help or contact a Poison Control Center right away (1-800-222-1222).

Directions

- chew or crush tablets completely before swallowing.

adults and children 6 years and over | chew 2 tablets daily; not more than 2 tablets in 24 hours
children 2 to under 6 years of age | chew 1 tablet daily; not more than 1 tablet in 24 hours
children under 2 years of age | ask a doctor
consumers with liver or kidney disease | ask a doctor

Other information

- Phenylketonurics: contains phenylalanine 1.25 mg per tablet.
- TAMPER EVIDENT: DO NOT USE IF BLISTER UNITS ARE TORN, BROKEN OR SHOW ANY SIGNS OF TAMPERING.
- store between 20° to 25°C (68° and 77°F).

Inactive ingredients

aspartame, citric acid anhydrous, colloidal silicon dioxide, D&C red No. 27 aluminum lake, FD&C blue No. 2 aluminum lake, flavor, magnesium stearate, mannitol, microcrystalline cellulose, sodium starch glycolate, stearic acid

Questions?

call toll-free Monday to Friday 8:30 am to 5:00 pm EST at 1-800-406-7984.

Keep the carton. It contains important information. See end panel for expiration date.

Distributed by:

Ohm Laboratories Inc.

New Brunswick, NJ 08901

0619

Principal Display Panel – 30 Chewable Tablet Blister Pack Carton

NDC 51660-753-31

†Compare to the active ingredient of Children’s Claritin® Chewable

ages 2 years and older

Children’s

Loratadine Chewable Tablets USP, 5 mg

Antihistamine

Indoor & Outdoor Allergies

30 CHEWABLE TABLETS

The chewable tablets are to be chewed before swallowing.

Grape Flavored

Non-Drowsy*

24 Hour Relief Of:

- Sneezing
- Runny Nose
- Itchy, Watery Eyes
- Itchy Nose or Throat

* When taken as directed. See Drug Facts Panel.

†Ohm® is a registered trademark of Sun Pharmaceutical Industries, Inc. All other trademarks are property of their respective owners.